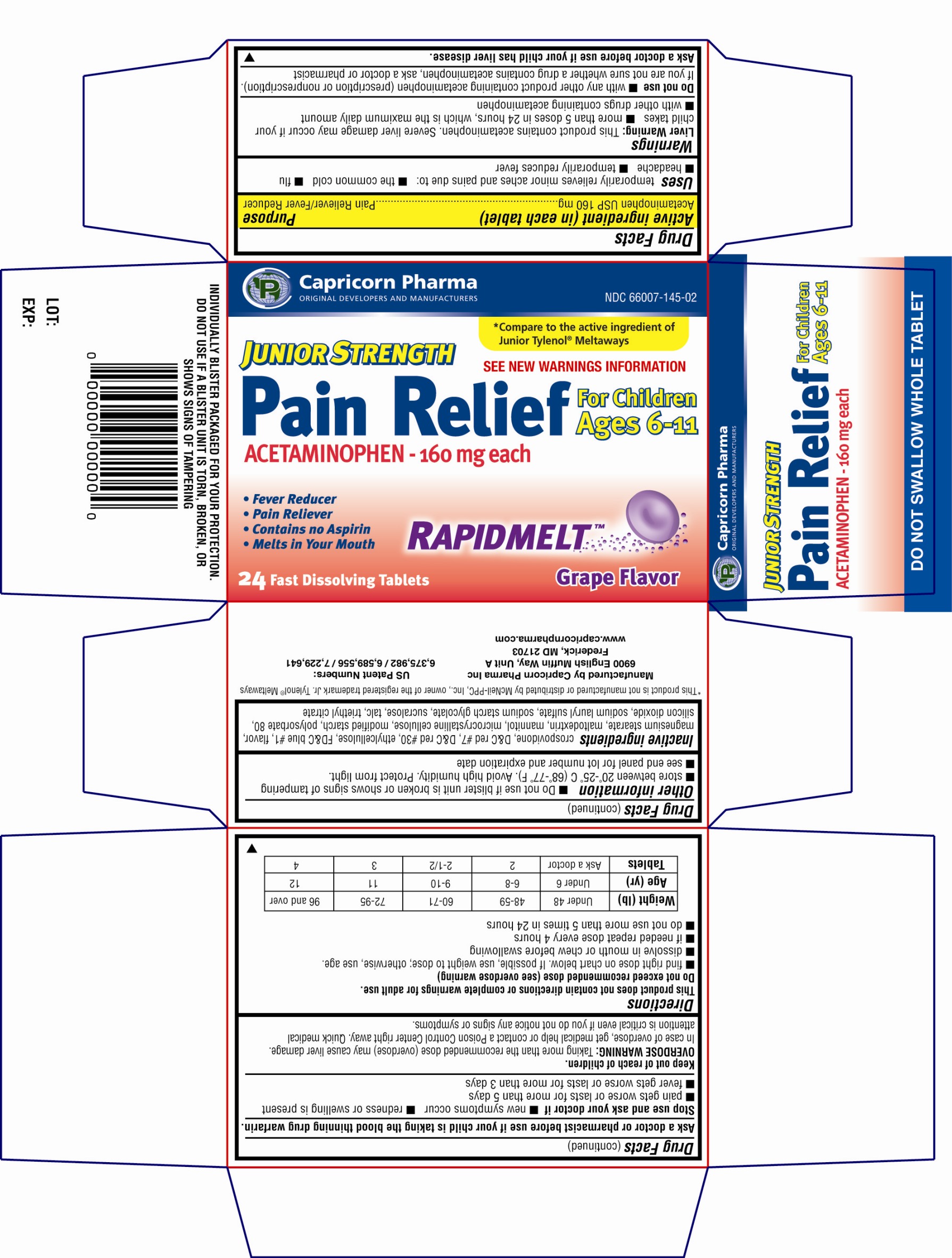 DRUG LABEL: Junior Strength Pain Relief
NDC: 66007-145 | Form: TABLET
Manufacturer: Capricorn Pharma Inc.
Category: otc | Type: HUMAN OTC DRUG LABEL
Date: 20100726

ACTIVE INGREDIENTS: ACETAMINOPHEN 160 mg/1 1

Drug Facts

Active Ingredient(in each tablet)

Acetaminophen 160mg

Purpose

Pain Reliever/Fever Reducer

Uses

temporarily relieves minor aches and pains due to:

■ the common cold

■ flu

■ headache

■ temporarily reduces fever

Warnings

Liver Warning: This product contains acetaminophen. Severe liver damage may occur if your child takes:
■ more than 5 doses in 24 hours, which is maximum daily amount
■ with other drugs containing acetaminophen

Do not use

■ with any other product containing acetaminophen (prescription or nonprescription). If you are not sure whether a drug contains acetaminophen, ask a doctor or pharmacist.

Ask a doctor before use if your child has liver disease.

Ask a doctor or pharmacist before use if your child is taking the blood thinning drug warfarin.

Stop use and ask doctor if

■ new symptoms occur
■ redness or swelling is present
■ pain gets worse or lasts for more than 5 days
■ fever gets worse or lasts for more than 3 days

Keep out of reach of children.

Overdose warning:

Taking more than the recommended dose (overdose) may cause liver damage. In case of overdose, get medical help or contact a Poison Control Center right away. Quick medical attention is critical even if you do not notice any signs or symptoms.

Directions

This product does not contain directions or complete warnings for adult use.
Do not exceed recommended dose (see overdose warning)
■ find right dose on chart below. If possible, use weight to dose; otherwise, use age
■ dissolve in mouth or chew before swallowing
■ if needed, repeat dose every 4 hours
■ do not use more than 5 times in 24 hours

Weight (lb) | Under 48 | 48-59 | 60-71 | 72-95 | 96 and over
Age (yr) | Under 6 | 6-8 | 9-10 | 11 | 12
Tablets | Ask a doctor | 2 | 2-1/2 | 3 | 4

Other Information

■ Do not use if blister unit is broken or shows signs of tampering.
■ Store between 20-25ºC (68-77ºF). Avoid high humidity. Protect from light.
■ See end panel for lot number and expiration date.

Inactive Ingredient

Crospovidone, D & C red # 7, D & C red # 30, ethylcellulose, FD & C blue # 1, flavor, magnesium stearate, maltodextrin, mannitol, microcrystalline cellulose, modified starch, polysorbate 80, silicon dioxide, sodium lauryl sulfate, sodium starch glycolate, sucralose, talc, triethyl citrate

Principal Display Panel

Capricorn Pharma
ORIGINAL DEVELOPERS AND MANUFACTURERS
Compare to the active ingredient of Junior Tylenol Meltaways
JUNIOR STRENGTH
Pain Relief
ACETAMINOPHEN - 160mg each
For Children Ages 6-11
See new warnings information
* Fever Reducer
* Pain Reliever
* Contains no Aspirin
* Melts in your mouth
RAPIDMELT
24 Fast Dissolving Tablets
Grape Flavor